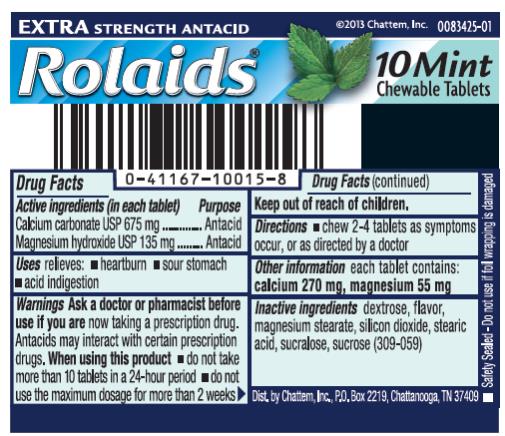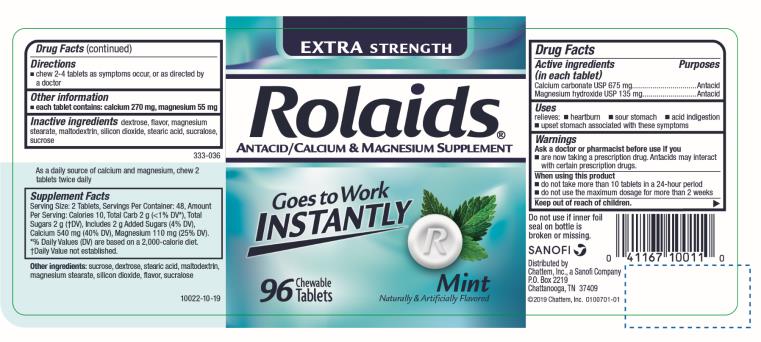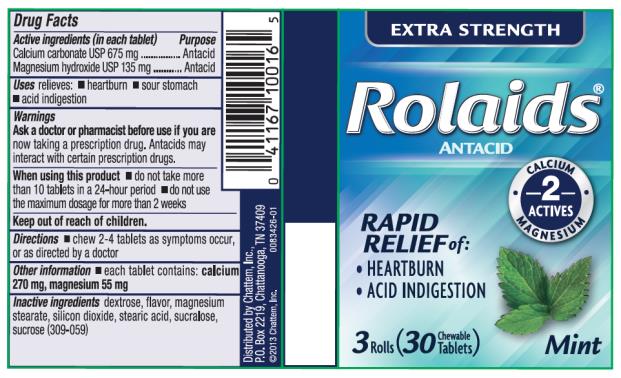 DRUG LABEL: Rolaids Extra Strength Mint
NDC: 41167-1001 | Form: TABLET, CHEWABLE
Manufacturer: Chattem, Inc.
Category: otc | Type: HUMAN OTC DRUG LABEL
Date: 20250115

ACTIVE INGREDIENTS: CALCIUM CARBONATE 675 mg/1 1; MAGNESIUM HYDROXIDE 135 mg/1 1
INACTIVE INGREDIENTS: DEXTROSE; MAGNESIUM STEARATE; SILICON DIOXIDE; STEARIC ACID; SUCRALOSE; SUCROSE; MALTODEXTRIN

Rolaids Extra Strength Tablets Mint

Extra Strength Antacid Rolaids Mint 10 Chewable Tablets

Drug Facts

Active ingredient

(in each tablet)
Calcium carbonate USP 675 mg
Magnesium hydroxide USP 135 mg

Purpose

Antacid

Use

relieves:

- heartburn
- sour stomach
- acid indigestion

Warnings

Ask a doctor or pharmacist before use if you are

now taking a prescription drug. Antacids may interact with certain prescription drugs.

When using this product

- do not take more than 10 tablets in a 24-hour period
- do not use the maximum dosage for more than 2 weeks

Directions

- chew 2-4 tablets as symptoms occur, or as directed by a doctor

Other information

each tablet contains: calcium 270 mg, magnesium 55 mg

Inactive ingredients

dextrose, flavor, magnesium stearate, silicon dioxide, stearic acid, sucralose, sucrose (309-059)
Dist. by CHATTEM, INC.
P.O. Box 2219
Chattanooga, TN 37409

Regular Strength Antacid Rolaids Mint 96 Chewable Tablets

Drug Facts

Active ingredient

(in each tablet)
Calcium carbonate USP 675 mg
Magnesium hydroxide USP 135 mg

Purpose

Antacid

Use

relieves:

- heartburn
- sour stomach
- acid indigestion

Warnings

Ask a doctor or pharmacist before use if you are

now taking a prescription drug. Antacids may interact with certain prescription drugs.

When using this product

- do not take more than 10 tablets in a 24-hour period
- do not use the maximum dosage for more than 2 weeks

Directions

- chew 2-4 tablets as symptoms occur, or as directed by a doctor

Other information

each tablet contains: calcium 270 mg, magnesium 55 mg

Inactive ingredients

dextrose, flavor, magnesium stearate, silicon dioxide, stearic acid, sucralose, sucrose (309-054)

As a daily source of calcium and magnesium, chew 2 tablets twice daily.

Supplement Facts
Serving Size: 2 Tablets, Servings Per Container: 48, Amount Per Serving: Calories 8, Total Carb 2 g (<1% DV*), Sugars 2 g (†DV), Calcium 540 mg (54% DV), Magnesium 110 mg (29% DV). *Percent Daily Values (DV) are based on a 2,000 calories diet.
†Daily Value not established.

Other ingredients

sucrose, dextrose, stearic acid, magnesium stearate, silicon dioxide, flavor, sucralose

Regular Strength Antacid Rolaids Mint 30 Chewable Tablets

Drug Facts

Active ingredient

(in each tablet)
Calcium carbonate USP 675 mg
Magnesium hydroxide USP 135 mg

Purpose

Antacid

Use

relieves:

- heartburn
- sour stomach
- acid indigestion

Warnings

Ask a doctor or pharmacist before use if you are

now taking a prescription drug. Antacids may interact with certain prescription drugs.

When using this product

- do not take more than 10 tablets in a 24-hour period
- do not use the maximum dosage for more than 2 weeks

Directions

- chew 2-4 tablets as symptoms occur, or as directed by a doctor

Other information

each tablet contains: calcium 270 mg, magnesium 55 mg

Inactive ingredients

dextrose, flavor, magnesium stearate, silicon dioxide, stearic acid, sucralose, sucrose (309-059)
Dist. by CHATTEM, INC.
P.O. Box 2219
Chattanooga, TN 37409

PRINCIPAL DISPLAY PANEL

EXTRA STRENGTH ANTACID
Rolaids®
10 Mint Chewable Tablets

PRINCIPAL DISPLAY PANEL

EXTRA STRENGTH ANTACID
Rolaids®
Rapid Relief of:
Heartburn
Acid Indigestion
96 Chewable Tablets
Mint

PRINCIPAL DISPLAY PANEL

EXTRA STRENGTH
Rolaids®
ANTACID
Rapid Relief of:
Heartburn
Acid Indigestion
3 Rolls
30 Chewable Tablets
Mint